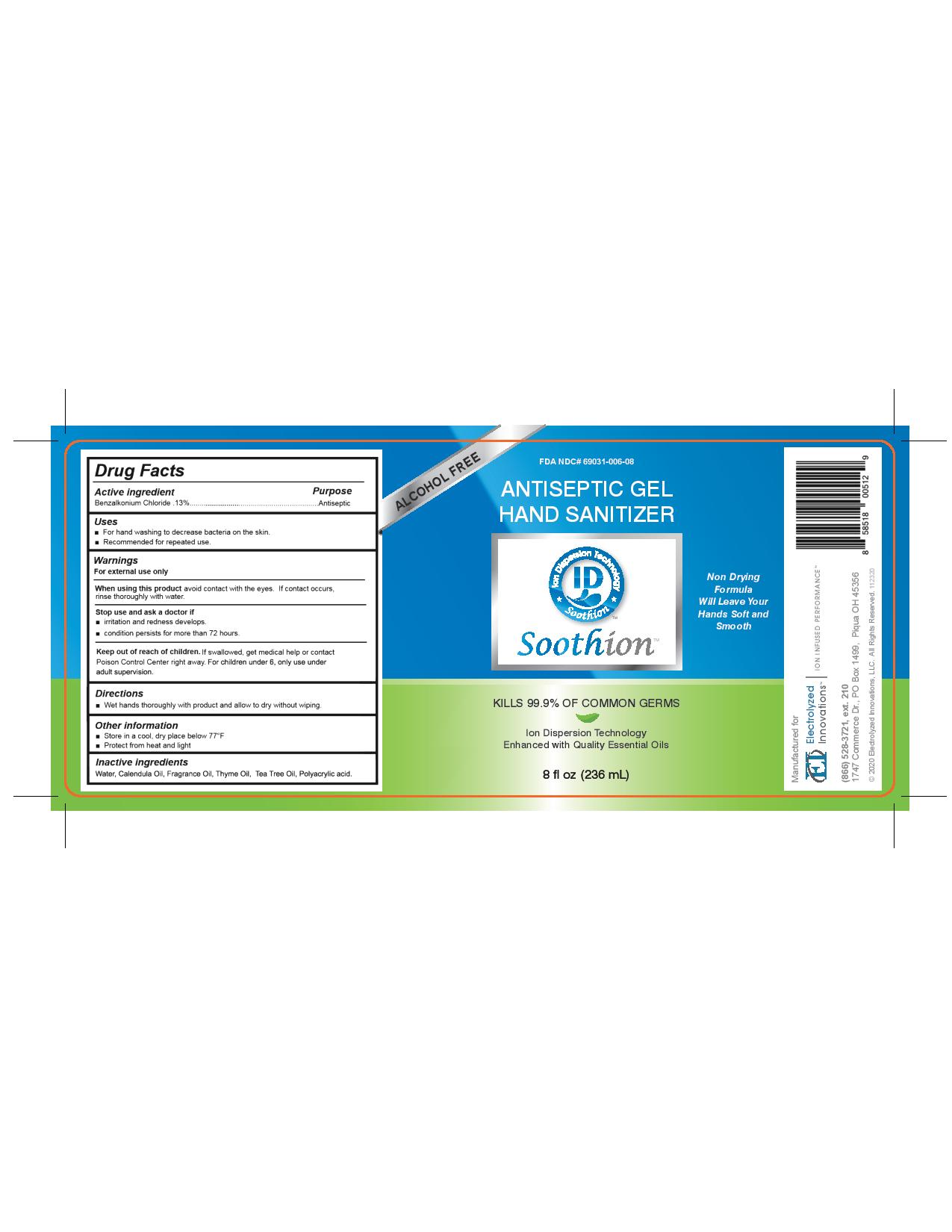 DRUG LABEL: Soothion Antiseptic Hand Sanitizer
NDC: 69031-006 | Form: LOTION
Manufacturer: Electrolyzed Innovations, LLC
Category: otc | Type: HUMAN OTC DRUG LABEL
Date: 20201202

ACTIVE INGREDIENTS: BENZALKONIUM CHLORIDE 0.13 g/100 g
INACTIVE INGREDIENTS: TEA TREE OIL; FRAGRANCE CLEAN ORC0600327; CALENDULA OFFICINALIS FLOWER; POLYACRYLIC ACID (250000 MW); THYME OIL; WATER

Drug Facts

Active ingredient

Benzalkonium Chloride 0.13%

Purpose

Antiseptic

Uses

- For hand washing to decrease bacteria on the skin.
- Recommended for repeated use.

Warnings

For external use only.

When using this product

avoid contact with the eyes. If contact occurs, rinse thoroughly with water.

Stop use and ask a doctor if

- irritation and redness develops
- condition persists for more than 72 hours.

Keep out of reach of children. If swallowed, get medical help or contact Poison Control Center immediately. For children under 6, only use under adult supervision.

Directions

- Wet hands thoroughly with product and allow to dry without wiping.

Other information

- Store in a cool, dry place below 77°F
- Protect from heat and light

Inactive ingredients

Water, Calendula Oil, Fragrance Oil, Thyme Oil, Tea Tree Oil, Polyacrylic Acid

DESCRIPTION

Questions? Call:
1-866-528-3721 ex. 210.
Mon-Fri 9AM to 5PM CST
Manufactured For
Electrolyzed Innovations, LLC
1747 Commerce Dr. P.O Box 1499

Piqua, OH 45356

Principal Display Panel

FDA NDC # 69031-006-08

Alcohol Free

Antiseptic Gel Hand Sanitizer

Soothion

Non Dyring Formula Will Leave Your Hands Soft and Smooth

Kills 99.9% of Common Germs

Ion Dispersion Technology

Enhanced with Quality Essential Oils

8 fl oz (236 mL)